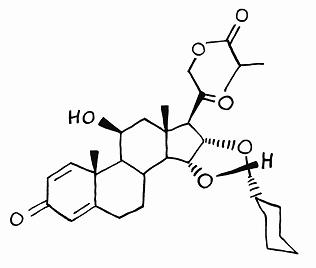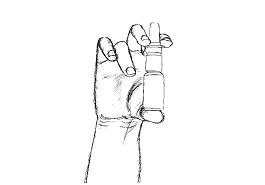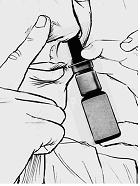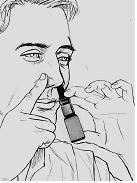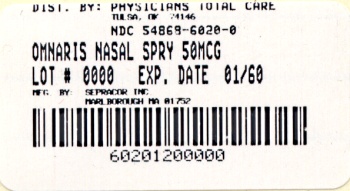 DRUG LABEL: Omnaris
NDC: 54868-6020 | Form: SPRAY
Manufacturer: Physicians Total Care, Inc.
Category: prescription | Type: HUMAN PRESCRIPTION DRUG LABEL
Date: 20100524

ACTIVE INGREDIENTS: CICLESONIDE 50 ug/1 1
INACTIVE INGREDIENTS: CELLULOSE, MICROCRYSTALLINE; CARBOXYMETHYLCELLULOSE SODIUM; HYPROMELLOSE; POTASSIUM SORBATE; EDETATE SODIUM; HYDROCHLORIC ACID

DESCRIPTION

The active component of OMNARIS Nasal Spray is ciclesonide, a non-halogenated glucocorticoid having the chemical name pregna -1,4-diene-3,20-dione, 16,17-[[R-cyclohexylmethylene]bis(oxy)]-11-hydroxy-21-(2-methyl-1-oxopropoxy)-,(11β,16α)-. Ciclesonide is delivered as the R-epimer. The empirical formula is C32H44O7 and its molecular weight is 540.7. Its structural formula is as follows:

Ciclesonide is a white to yellow-white powder, practically insoluble in water and freely soluble in ethanol and acetone. OMNARIS Nasal Spray is a metered-dose, manual-pump spray formulation containing a hypotonic aqueous suspension of ciclesonide. OMNARIS Nasal Spray also contains microcrystalline cellulose, carboxymethylcellulose sodium, hypromellose, potassium sorbate and edetate sodium; and hydrochloric acid to adjust the pH to 4.5. The contents of one 12.5 gram bottle provide 120 actuations, after initial priming. Prior to initial use, OMNARIS Nasal Spray must be gently shaken and then the pump must be primed by actuating eight times. Once primed, each actuation of the pump delivers 50 mcg ciclesonide in a volume of 70 microliters from the nasal actuator. If the product is not used for four consecutive days, it should be gently shaken and reprimed with one spray or until a fine mist appears.

CLINICAL PHARMACOLOGY

Mechanism of Action

Ciclesonide is a pro-drug that is enzymatically hydrolyzed to a pharmacologically active metabolite, C21-desisobutyryl-ciclesonide (des-ciclesonide or RM1) following intranasal application. Des-ciclesonide has anti-inflammatory activity with affinity for the glucocorticoid receptor that is 120 times higher than the parent compound.

The precise mechanism through which ciclesonide affects allergic rhinitis symptoms is not known. Corticosteroids have been shown to have a wide range of effects on multiple cell types (e.g., mast cells, eosinophils, neutrophils, macrophages, and lymphocytes) and mediators (e.g., histamine, eicosanoids, leukotrienes, and cytokines) involved in allergic inflammation.

Pharmacokinetics

Absorption

Ciclesonide and des-ciclesonide have negligible oral bioavailability (both less than 1%) due to low gastrointestinal absorption and high first-pass metabolism. The intranasal administration of ciclesonide at recommended doses results in negligible serum concentrations of ciclesonide. However, the known active metabolite (des-ciclesonide) is detected in the serum of some patients after nasal inhalation of ciclesonide. The bioanalytical assay used has a lower limit of quantification of 25 pg/mL and 10 pg/mL, for ciclesonide and des-ciclesonide, respectively

In healthy adults treated for two weeks with 50 to 800 mcg of ciclesonide nasal spray daily (n=6 in each treatment group), the peak serum concentrations of des-ciclesonide in all subjects were found to be below 30 pg/mL. Of those treated with 800 mcg and 400 mcg daily, 100% and 67% had detectable levels of des-ciclesonide, respectively. With daily doses of 200 mcg or less, detectable serum levels of des-ciclesonide were not observed.

In pediatric subjects treated with 25 to 200 mcg of ciclesonide nasal spray daily, serum concentrations of des-ciclesonide were below 45 pg/mL, with the exception of one value of 64.5 pg/mL. In a 12-week study in children 6 to 11 years of age with perennial allergic rhinitis, des-ciclesonide was detected in 50% of the subjects treated with 200 mcg and in 5% of those treated with 100 mcg ciclesonide nasal spray daily. In a 6-week study in children 2 to 5 years of age with perennial allergic rhinitis, des-ciclesonide was detected in 41%, 22%, and 13% of the subjects treated with 200 mcg, 100 mcg, and 25 mcg ciclesonide nasal spray daily, respectively.

Distribution

Following intravenous administration of 800 mcg of ciclesonide, the volumes of distribution of ciclesonide and des-ciclesonide were approximately 2.9 L/kg and 12.1 L/kg, respectively. The percentage of ciclesonide and des-ciclesonide bound to human plasma proteins averaged ≥ 99% each, with ≤ 1% of unbound drug detected in the systemic circulation. Des-ciclesonide is not significantly bound to human transcortin.

Metabolism

Intranasal ciclesonide is hydrolyzed to a biologically active metabolite, des-ciclesonide, by esterases in the nasal mucosa. Des-ciclesonide undergoes further metabolism in the liver to additional metabolites mainly by the cytochrome P450 (CYP) 3A4 isozyme and to a lesser extent by CYP 2D6. The full range of potentially active metabolites of ciclesonide has not been characterized. After intravenous administration of ^14C-ciclesonide, 19.3% of the resulting radioactivity in the plasma is accounted for by ciclesonide or des-ciclesonide; the remainder may be a result of other, as yet, unidentified multiple metabolites.

Elimination

Following intravenous administration of 800 mcg of ciclesonide, the clearance values of ciclesonide and des-ciclesonide were high (approximately 152 L/h and 228 L/h, respectively). ^14C-labeled ciclesonide was predominantly excreted via the feces after intravenous administration (66%) indicating that excretion through bile is the major route of elimination. Approximately 20% or less of drug related radioactivity was excreted in the urine.

Special Populations

The pharmacokinetics of intranasally administered ciclesonide have not been assessed in patient subpopulations because the resulting blood levels of ciclesonide and des-ciclesonide are insufficient for pharmacokinetic calculations. However, population pharmacokinetic analysis showed that characteristics of des-ciclesonide after oral inhalation of ciclesonide were not appreciably influenced by a variety of subject characteristics such as body weight, age, race, and gender. Compared to healthy subjects, the systemic exposure (Cmax and AUC) in patients with liver impairment increased in the range of 1.4 to 2.7 fold after 1280 mcg ex-actuator ciclesonide by oral inhalation and dose adjustment in liver impairment is not necessary. Studies in renal impaired patients were not conducted.

Pharmacodynamics

In a 12-week study in children 6-11 years of age with perennial allergic rhinitis, daily doses of 200 mcg, 100 mcg, and 25 mcg of OMNARIS Nasal Spray were compared to placebo nasal spray. Adrenal function was assessed by measurement of 24-hour urinary free cortisol (in 32 to 44 patients per group) and morning plasma cortisol levels (in 45 to 61 patients per group) before and after 12 consecutive weeks of treatment. The ciclesonide-treated groups had a numerically greater decline in 24-hour urinary free cortisol compared to the placebo treated group. The differences (and 95% confidence intervals) from placebo in the mean change from baseline to 12 weeks were -0.81 (-4.0, 2.4), -0.08 (-3.1, 2.9), and -2.11 (-5.3, 1.1) mcg/day for 200 mcg, 100 mcg, and 25 mcg dose groups, respectively. The mean AM plasma cortisol value did not show any consistent treatment effect with differences (and 95% confidence intervals) from placebo in the mean change from baseline to 12 weeks of 0.35 (-1.4, 2.1), 0.12 (-1.5, 1.7), and -0.38 (-2.1, 1.3) mcg/dL for 200 mcg, 100 mcg, and 25 mcg dose groups respectively. In this study, serum was assayed for ciclesonide and des-ciclesonide (see CLINICAL PHARMACOLOGY: Pharmacokinetics: Absorption).

In a 6-week study in children 2 to 5 years of age with perennial allergic rhinitis, daily doses of 200 mcg, 100 mcg, and 25 mcg of OMNARIS Nasal Spray were compared to placebo nasal spray. Adrenal function was assessed by measurement of 24-hour urinary free cortisol (in 15 to 22 patients per group) and morning plasma cortisol levels (in 28 to 30 patients per group) before and after 6 consecutive weeks of treatment. The ciclesonide-treated groups had a numerically greater decline in 24-hour urinary free cortisol compared to the placebo treated group. The differences (and 95% confidence intervals) from placebo in the mean change from baseline to 6 weeks were -2.04 (-4.4, 0.3), -1.96 (-4.5, 0.6), and -1.76 (-4.3, 0.8) mcg/day for the 200 mcg, 100 mcg, and 25 mcg dose groups, respectively. The plasma cortisol also decreased numerically after treatment with ciclesonide. The differences (and 95% confidence intervals) from placebo in the mean change in plasma cortisol from baseline to 6 weeks were -1.04 (-2.7, 0.7), -0.36 (-2.1, 1.4), and -0.12 (-1.8, 1.6) mcg/dL for the 200 mcg, 100 mcg, and 25 mcg dose groups, respectively. In this study, serum was assayed for ciclesonide and des-ciclesonide (see CLINICAL PHARMACOLOGY: Pharmacokinetics: Absorption).

There are no adequately conducted studies in adults and adolescents that assess the effect of OMNARIS Nasal Spray on adrenal function.

CLINICAL TRIALS

Seasonal and Perennial Allergic Rhinitis

Adult and Adolescent Patients Aged 12 Years and Older:

The efficacy and safety of OMNARIS Nasal Spray were evaluated in 4 randomized, double-blind, parallel-group, multicenter, placebo-controlled clinical trials of 2 weeks to 1 year in duration conducted in the United States and Canada in adolescents and adults with allergic rhinitis. Three of these trials were 2 to 6 weeks in duration and primarily designed to assess efficacy. One of these trials was 1 year in duration and primarily designed to assess safety. The three trials of 2 to 6 weeks duration included a total of 1524 patients (495 males and 1029 females) of whom 79 were adolescents, ages 12 to 17 years. Of the 1524 patients, 546 patients received OMNARIS Nasal Spray 200 mcg once daily administered as 2 sprays in each nostril. Patients enrolled in the studies were 12 to 86 years of age with a history of seasonal or perennial allergic rhinitis, a positive skin test to at least one relevant allergen, and active symptoms of allergic rhinitis at study entry. Assessment of efficacy in these trials was based on patient recording of four nasal symptoms (runny nose, nasal itching, sneezing, and nasal congestion) on a 0-3 categorical severity scale (0=absent, 1=mild, 2=moderate, and 3=severe) as reflective or instantaneous scores. Reflective scoring required the patients to record symptom severity over the previous 12 hours; the instantaneous scoring required patients to record symptom severity at the time of recording. The results of these trials showed that patients treated with OMNARIS Nasal Spray 200 mcg once daily exhibited statistically significantly greater decreases in total nasal symptom scores than placebo treated patients. Secondary measures of efficacy were also generally supportive.

Of the three trials primarily designed to assess efficacy, one was a 2-week dose-ranging trial that evaluated efficacy of four doses of OMNARIS Nasal Spray in patients with seasonal allergic rhinitis. The primary efficacy endpoint was the difference from placebo in the change from baseline of the sum of morning and evening reflective total nasal symptom score averaged over the 2-week treatment period. Results of the primary efficacy endpoint are shown in Table 1. In this trial OMNARIS Nasal Spray 200 mcg once daily was statistically significantly different from placebo, but the lower doses were not statistically significantly different from placebo.

Table 1 Mean change in reflective total nasal symptom score over 2 weeks in patients with seasonal allergic rhinitis
Treatment | N | Baseline* | Change from Baseline | Difference Estimate | from Placebo 95% CI | p-value
Seasonal Allergic Rhinits Trial - Reflective total nasal symptoms score
Ciclesonide 200 mcg | 144 | 18.8 | -5.73 | -1.35 | (-2.43, -0.28) | 0.014
Ciclesonide 100 mcg | 145 | 18.7 | -5.26 | -0.88 | (-1.96, 0.19) | 0.11
Ciclesonide 50 mcg | 143 | 18.4 | -4.82 | -0.44 | (-1.52, 0.63) | 0.42
Ciclesonide 25 mcg | 146 | 18.7 | -4.74 | -0.35 | (-1.42, 0.71) | 0.51
Placebo | 148 | 17.8 | -4.38

* Sum of AM and PM
Scores; Maximum score = 24
Of the other trials primarily designed to assess efficacy, one was a 4-week single dose-level trial conducted in patients with seasonal allergic rhinitis and the other was a 6-week single dose-level trial conducted in patients with perennial allergic rhinitis. The primary efficacy endpoint in the seasonal allergic rhinitis trial was the difference from placebo in the change from baseline of the average of morning and evening reflective total nasal symptom score averaged over the first 2 weeks of treatment. The primary efficacy endpoint in the perennial allergic rhinitis trial was the difference from placebo in the change from baseline of the average of morning and evening reflective total nasal symptom score averaged over the 6 weeks of treatment. Efficacy results of these two trials are shown in Table 2. In these trials, OMNARIS Nasal Spray 200 mcg once daily was statistically significantly different from placebo. Statistically significant differences in the morning pre-dose instantaneous total nasal symptom score indicate that the effect was maintained over the full 24-hour dosing interval.

Table 2 Mean changes in reflective total nasal symptom score and instantaneous total nasal symptom score in allergic rhinitis trials
Treatment | n | Baseline* | Change from Baseline | Estimate | Difference 95% CI | from Placebo p-value
Seasonal Allergic Rhinitis Trial - Reflective total nasal symptom score
Ciclesonide 200 mcg | 162 | 8.96 | -2.40 | -0.90 | (-1.36, -0.45) | less than 0.001
Placebo | 162 | 8.83 | -1.50
Seasonal Allergic Rhinitis Trial - Instantaneous total nasal symptom score
Ciclesonide 200 mcg | 162 | 8.45 | -1.87 | -0.84 | (-1.30, -0.39) | less than 0.001
Placebo | 162 | 8.33 | -1.03
Perennial Allergic Rhinitis Trial - Reflective total nasal symptom score
Ciclesonide 200 mcg | 232 | 7.59 | -2.51 | -0.62 | (-0.97, -0.28) | less than 0.001
Placebo | 229 | 7.72 | -1.89
Perennial Allergic Rhinitis Trial - Instantaneous total nasal symptom score
Ciclesonide 200 mcg | 232 | 7.05 | -1.99 | -0.53 | (-0.90, -0.17) | 0.004
Placebo | 229 | 7.05 | -1.46

* Mean of AM and PM score from reflective total nasal symptom score; Mean of AM score for instantaneous total nasal symptom score; Maximum = 12

Onset of action was evaluated in two environmental exposure unit studies with a single dose of OMNARIS Nasal Spray 200 mcg. Results from these two studies did not demonstrate a replicate onset of action within the assessment period. Onset of action was also evaluated in the 4-week seasonal allergic rhinitis and in the 6-week perennial allergic rhinitis trial by frequent recording of instantaneous symptom score after the first dose. In these trials, onset of effect was seen within 24 to 48 hours with further symptomatic improvement observed over 1 to 2 weeks in seasonal allergic rhinitis and 5 weeks in perennial allergic rhinitis.

Pediatric Patients Aged 6 to 11 Years:

The efficacy of OMNARIS Nasal Spray was evaluated in two randomized, double-blind, parallel-group, multicenter, placebo-controlled clinical trials of 2 and 12 weeks in duration in 1282 patients 6 to 11 years of age with allergic rhinitis. Of the two trials, one was 2 weeks in duration conducted in patients with seasonal allergic rhinitis that evaluated efficacy of 200 mcg and 100 mcg of OMNARIS nasal spray once daily. The other trial was 12 weeks in duration conducted in patients with perennial allergic rhinitis that evaluated efficacy of 200 mcg, 100 mcg, and 25 mcg of OMNARIS nasal spray once daily. Of the total number of patients enrolled in the 2 studies, 380 were treated with 200 mcg of OMNARIS nasal spray once daily. The primary efficacy endpoint was the difference from placebo in the change from baseline of the average of morning and evening reflective total nasal symptom score averaged over 2 weeks of treatment in the seasonal allergic rhinitis trial and over the first 6 weeks of treatment in the perennial allergic rhinitis trial. In the 2-week trial in patients with seasonal allergic rhinitis, the OMNARIS Nasal Spray 200 mcg once daily dose was statistically significantly different from placebo, but the 100 mcg once daily dose was not statistically significantly different from placebo. The efficacy results for the seasonal allergic rhinitis trial are shown in Table 3.

Table 3 Mean changes in reflective total nasal symptom score in 1 seasonal allergic rhinitis trial in children 6 to 11 years of age.
Treatment | n | Baseline* | Change from Baseline | Estimate | Difference 95% CI | from Placebo p-value
Reflective total nasal symptom score
Ciclesonide 200 mcg | 215 | 8.25 | -2.46 | -0.39 | (-0.76, -0.02) | 0.040
Ciclesonide 100 mcg | 199 | 8.41 | -2.38 | -0.32 | (-0.69, 0.06) | 0.103
Placebo | 204 | 8.41 | -2.07

* Mean of AM and PM score from reflective total nasal symptom score; Maximum = 12

In the 12-week trial in patients with perennial allergic rhinitis, none of the ciclesonide doses were statistically significantly different from placebo. The means and 95% confidence intervals for the differences (OMNARIS Nasal Spray minus placebo) between OMNARIS Nasal Spray 200 mcg, 100 mcg, and 25 mcg treatment groups and placebo were -0.31 (-0.75, 0.13), 0.02 (-0.41, 0.46), and 0.09 (-0.35, 0.53), respectively.

Pediatric Patients Aged 2 to 5 Years:

Efficacy of OMNARIS Nasal Spray in patients 2 to 5 years of age has not been established (See PRECAUTIONS: Pediatric Use).

INDICATIONS AND USAGE

Seasonal Allergic Rhinitis

OMNARIS Nasal Spray is indicated for the treatment of nasal symptoms associated with seasonal allergic rhinitis in adults and children 6 years of age and older.

Perennial Allergic Rhinitis

OMNARIS Nasal Spray is indicated for the treatment of nasal symptoms associated with perennial allergic rhinitis in adults and adolescents 12 years of age and older.

CONTRAINDICATIONS

OMNARIS Nasal Spray is contraindicated in patients with a hypersensitivity to any of its ingredients.

WARNINGS

The replacement of a systemic corticosteroid with a topical corticosteroid can be accompanied by signs of adrenal insufficiency. In addition, some patients may experience symptoms of corticosteroid withdrawal, e.g., joint and/or muscular pain, lassitude, and depression. Patients previously treated for prolonged periods with systemic corticosteroids and transferred to topical corticosteroids should be carefully monitored for acute adrenal insufficiency in response to stress. In those patients who have asthma or other clinical conditions requiring long-term systemic corticosteroid treatment, rapid decreases in systemic corticosteroid dosages may cause a severe exacerbation of their symptoms.

Patients who are using drugs that suppress the immune system are more susceptible to infections than healthy individuals. Chickenpox and measles, for example, can have a more serious or even fatal course in children or adults using corticosteroids. In children or adults who have not had these diseases or been properly immunized, particular care should be taken to avoid exposure. How the dose, route, and duration of corticosteroid administration affect the risk of developing a disseminated infection is not known. The contribution of the underlying disease and/or prior corticosteroid treatment to the risk is also not known. If exposed to chickenpox, prophylaxis with varicella zoster immune globulin (VZIG) may be indicated. If exposed to measles, prophylaxis with pooled intramuscular immunoglobulin (IG) may be indicated. (See the respective package inserts for complete VZIG and IG prescribing information). If chickenpox develops, treatment with antiviral agents may be considered.

PRECAUTIONS

General

Intranasal corticosteroids may cause a reduction in growth velocity when administered to pediatric patients (see PRECAUTIONS: Pediatric Use). Rarely, immediate hypersensitivity reactions or contact dermatitis may occur after the administration of intranasal corticosteroids. Patients with a known hypersensitivity reaction to other corticosteroid preparations should use caution when using ciclesonide nasal spray since cross reactivity to other corticosteroids including ciclesonide may also occur.

Because of the inhibitory effect of corticosteroids on wound healing, patients who have experienced recent nasal septal ulcers, nasal surgery, or nasal trauma should not use a nasal corticosteroid until healing has occurred. In clinical studies with OMNARIS Nasal Spray, the development of localized infections of the nose and pharynx with Candida albicans has rarely occurred. When such an infection develops, it may require treatment with appropriate local therapy and discontinuation of OMNARIS Nasal Spray. Therefore, patients using OMNARIS Nasal Spray over several months or longer should be examined periodically for evidence of Candida infection or other signs of adverse effects on the nasal mucosa. Intranasal corticosteroids should be used with caution, if at all, in patients with active or quiescent tuberculosis infections of the respiratory tract; or in patients with untreated local or systemic fungal or bacterial infections; systemic viral or parasitic infections; or ocular herpes simplex.

If recommended doses of intranasal corticosteroids are exceeded or if individuals are particularly sensitive or predisposed by virtue of recent systemic steroid therapy, symptoms of hypercorticism may occur, including very rare cases of menstrual irregularities, acneiform lesions, and cushingoid features. If such changes occur, topical corticosteroids should be discontinued slowly, consistent with accepted procedures for discontinuing oral steroid therapy.

The risk of glaucoma was evaluated by assessments of intraocular pressure in 3 studies including 943 patients. Of these, 390 adolescents or adults were treated for up to 52 weeks and 186 children ages 2 to 11 received treatment with OMNARIS Nasal Spray 200 mcg daily for up to 12 weeks. In these trials, no significant differences in intraocular pressure changes were observed between OMNARIS Nasal Spray 200 mcg and placebo-treated patients. Additionally, no significant differences between OMNARIS Nasal Spray 200 mcg and placebo-treated patients were noted during the 52-week study of adults and adolescent patients in whom thorough ophthalmologic assessments were performed including evaluation of cataract formation using slit lamp examinations. Rare instances of wheezing, nasal septum perforation, cataracts, glaucoma, and increased intraocular pressure have been reported following the intranasal application of corticosteroids. Close follow-up is warranted in patients with a change in vision and with a history of glaucoma and/or cataracts.

Information for Patients

Patients being treated with OMNARIS Nasal Spray should receive the following information and instructions. This information is intended to aid them in the safe and effective use of this medication. It is not a disclosure of all possible adverse or intended effects.

Patients who are on immunosuppressive doses of corticosteroids should be warned to avoid exposure to chickenpox or measles, and if exposed, to obtain medical advice. Patients should use OMNARIS Nasal Spray at regular intervals since its effectiveness depends on its regular use (See DOSAGE AND ADMINISTRATION).

In clinical trials, the onset of effect was seen within 24 to 48 hours with further symptomatic improvement observed over 1 to 2 weeks in seasonal allergic rhinitis and 5 weeks in perennial allergic rhinitis. Initial assessment of response should be made during this timeframe and periodically until the patients symptoms are stabilized.

The patient should take the medication as directed and should not exceed the prescribed dosage. The patient should contact the physician if symptoms do not improve by a reasonable time or if the condition worsens. For the proper use of this unit and to attain maximum improvement, the patients should read and follow the accompanying patient instructions carefully. Spraying OMNARIS Nasal Spray directly into the eyes or onto the nasal septum should be avoided. It is important that the bottle is gently shaken prior to use to ensure that a consistent amount is dispensed per actuation. The bottle should be discarded after 120 actuations following initial priming or after 4 months after the bottle is removed from the foil pouch, whichever occurs first.

Drug Interactions

Based on in vitro studies in human liver microsomes, des-ciclesonide appears to have no inhibitory or induction potential on the metabolism of other drugs metabolized by CYP 450 enzymes. The inhibitory potential of ciclesonide on CYP450 isoenzymes has not been studied. In vitro studies demonstrated that the plasma protein binding of des-ciclesonide was not affected by warfarin or salicylic acid, indicating no potential for protein binding-based drug interactions.

In a drug interaction study, co-administration of orally inhaled ciclesonide and oral erythromycin, an inhibitor of cytochrome P450 3A4, had no effect on the pharmacokinetics of either des-ciclesonide or erythromycin. In another drug interaction study, co-administration of orally inhaled ciclesonide and oral ketoconazole, a potent inhibitor of cytochrome P450 3A4, increased the exposure (AUC) of des-ciclesonide by approximately 3.6-fold at steady state, while levels of ciclesonide remained unchanged. Therefore, ketoconazole should be administered with caution with intranasal ciclesonide.

Carcinogenesis, Mutagenesis, Impairment of Fertility

Ciclesonide demonstrated no carcinogenic potential in a study of oral doses up to 900 mcg/kg (approximately 20 and 10 times the maximum human daily intranasal dose in adults and children, respectively, based on mcg/m^2) in mice for 104 weeks and in a study of inhalation doses up to 193 mcg/kg (approximately 8 and 5 times the maximum human daily intranasal dose in adults and children, respectively, based on mcg/m^2) in rats for 104 weeks. Ciclesonide was not mutagenic in an Ames test or in a forward mutation assay and was not clastogenic in a human lymphocyte assay or in an in vitro micronucleus test. However, ciclesonide was clastogenic in the in vivo mouse micronucleus test. The concurrent reference corticosteroid (dexamethasone) in this study showed similar findings. No evidence of impairment of fertility was observed in a reproductive study conducted in male and female rats both dosed orally up to 900 mcg/kg/day (approximately 35 times the maximum human daily intranasal dose in adults based on mcg/m^2).

Pregnancy: Teratogenic Effects

Pregnancy Category C

Oral administration of ciclesonide in rats up to 900 mcg/kg (approximately 35 times the maximum human daily intranasal dose in adults based on mcg/m^2) produced no teratogenicity or other fetal effects. However, subcutaneous administration of ciclesonide in rabbits at 5 mcg/kg (less than the maximum human daily intranasal dose in adults based on mcg/m^2) or greater produced fetal toxicity. This included fetal loss, reduced fetal weight, cleft palate, skeletal abnormalities including incomplete ossifications, and skin effects. No toxicity was observed at 1 mcg/kg (less than the maximum human daily intranasal dose based on mcg/m^2).

There are no adequate and well-controlled studies in pregnant women. OMNARIS Nasal Spray, like other corticosteroids, should be used during pregnancy only if the potential benefit justifies the potential risk to the fetus. Experience with oral corticosteroids since their introduction in pharmacologic, as opposed to physiologic, doses suggests that rodents are more prone to teratogenic effects from corticosteroids than humans. In addition, because there is a natural increase in corticosteroid production during pregnancy, most women will require a lower exogenous corticosteroid dose and many will not need corticosteroid treatment during pregnancy.

Nonteratogenic effects

Hypoadrenalism may occur in infants born of mothers receiving corticosteroids during pregnancy. Such infants should be carefully monitored.

Nursing Mothers

It is not known if ciclesonide is excreted in human milk. However, other corticosteroids are excreted in human milk. In a study with lactating rats, minimal but detectable levels of ciclesonide were recovered in milk. Caution should be used when OMNARIS Nasal Spray is administered to nursing women.

Pediatric Use

The safety and effectiveness for seasonal and perennial allergic rhinitis in children 12 years of age and older have been established. The efficacy of OMNARIS Nasal Spray in patients 6 to 11 years of age for treatment of the symptoms of seasonal allergic rhinitis is supported by evidence from four adequate and well-controlled studies in adults and adolescents 12 years of age and older with seasonal and perennial allergic rhinitis, and one study in patients 6 to 11 years of age with seasonal allergic rhinitis. The efficacy of OMNARIS Nasal Spray for the treatment of the symptoms of perennial allergic rhinitis in patient 6 to 11 years of age has not been established (see CLINICAL TRIALS: Pediatric Patients Aged 6 to 11 Years). The efficacy of OMNARIS Nasal Spray in children 2 to 5 years of age has not been established. The safety of OMNARIS Nasal Spray in children 2 to 11 years of age was evaluated in 4 controlled clinical studies of 2 to 12 weeks duration (See CLINICAL PHARMACOLOGY: Pharmacodynamics, CLINICAL TRIALS, ADVERSE REACTIONS: Pediatric Patients).

Clinical studies in children less than two years of age have not been conducted. Studies in children under 2 years of age are waived because of local and systemic safety concerns.

Controlled clinical studies have shown that intranasal corticosteroids may cause a reduction in growth velocity in pediatric patients. This effect has been observed in the absence of laboratory evidence of hypothalamic-pituitary-adrenal (HPA)-axis suppression, suggesting that growth velocity is a more sensitive indicator of systemic corticosteroid exposure in pediatric patients than some commonly used tests of HPA-axis function. The long-term effects of this reduction in growth velocity associated with intranasal corticosteroids, including the impact on final adult height, are unknown. The potential for "catch-up" growth following discontinuation of treatment with intranasal corticosteroids has not been adequately studied. The growth of pediatric patients receiving intranasal corticosteroids, including OMNARIS Nasal Spray, should be monitored routinely (e.g., via stadiometry). The potential growth effects of prolonged treatment should be weighed against clinical benefits obtained and the availability of safe and effective noncorticosteroid treatment alternatives. To minimize the systemic effects of intranasal corticosteroids, each patient should be titrated to the lowest dose that effectively controls his/her symptoms.

Geriatric Use

Clinical studies of OMNARIS Nasal Spray did not include sufficient numbers of subjects age 65 and over to determine whether they respond differently from younger subjects. Other reported clinical experience has not identified differences in responses between the elderly and younger patients. In general, dose selection for an elderly patient should be cautious, usually starting at the low end of the dosing range, reflecting the greater frequency of decreased hepatic, renal, or cardiac function, and of concomitant disease or other drug therapy.

ADVERSE REACTIONS

Adult and Adolescent Patients Aged 12 Years and Older:

In controlled clinical studies conducted in the US and Canada, a total of 1524 patients ages 12 years and older received treatment with ciclesonide administered intranasally. In studies of 2 to 6 weeks duration in patients 12 years and older, 546 patients were treated with OMNARIS Nasal Spray 200 mcg daily, and in a study of up to one year in duration, 441 patients were treated with OMNARIS Nasal Spray 200 mcg daily. The overall incidence of adverse events for patients treated with OMNARIS Nasal Spray was comparable to that in patients treated with placebo. Adverse events did not differ appreciably based on age, gender, or race. Approximately 2% of patients treated with OMNARIS Nasal Spray 200 mcg in clinical trials discontinued because of adverse events; this rate was similar for patients treated with placebo. Table 4 displays adverse events, irrespective of drug relationship, that occurred with an incidence of 2% or greater and more frequently with OMNARIS Nasal Spray 200 mcg than with placebo in clinical trials of 2 to 6 weeks in duration.

Table 4 Adverse Events from Controlled Clinical Trials 2 to 6 Weeks in Duration in Patients 12 Years of Age and Older with Seasonal or Perennial Allergic Rhinitis
Adverse Event | OMNARIS Nasal Spray 200 mcg Once Daily (N =546) % | Placebo (N = 544) %
Headache | 6.0 | 4.6
Epistaxis | 4.9 | 2.9
Nasopharyngitis | 3.7 | 3.3
Ear Pain | 2.2 | 0.6

In a 52-week long-term safety trial that included 663 adults and adolescent patients (441 treated with ciclesonide: 227 males and 436 females) with perennial allergic rhinitis, the adverse event profile over the treatment period was similar to the adverse event profile in trials of shorter duration. Adverse events considered likely or definitely related to OMNARIS Nasal Spray that were reported at an incidence of 1% or greater of patients and more commonly in OMNARIS Nasal Spray versus placebo were epistaxis, nasal discomfort, and headache. No patient experienced a nasal septal perforation or nasal ulcer during long-term use of OMNARIS Nasal Spray. While primarily designed to assess the long-term safety of OMNARIS Nasal Spray 200 mcg once daily, this 52-week trial demonstrated greater decreases in total nasal symptom scores with OMNARIS Nasal Spray versus placebo treated patients over the entire treatment period.

Pediatric Patients Aged 6 to 11 Years:

Two controlled clinical studies 2 and 12 weeks in duration were conducted in the US and Canada and included a total of 1282 patients with allergic rhinitis ages 6 to 11 years, of which 913 were treated with OMNARIS (ciclesonide) Nasal Spray 200 mcg, 100 mcg or 25 mcg daily. The overall incidence of adverse events for patients treated with OMNARIS Nasal Spray was comparable to that in patients treated with placebo. Adverse events did not differ appreciably based on age, gender, or race. In clinical trials, 1.6% and 2.7% of patients treated with OMNARIS Nasal Spray 200 mcg or 100 mcg, respectively, discontinued because of adverse events; these rates were lower than the rate in patients treated with placebo (2.8%). Table 5 displays adverse events, irrespective of drug relationship, that occurred with an incidence of 3% or greater and more frequently with OMNARIS Nasal Spray 200 mcg than with placebo.

Table 5 Adverse Events from Controlled Clinical Trials 2 to 12 Weeks in Duration in Patients 6 to 11 Years of Age and Older with Seasonal or Perennial Allergic Rhinitis
Adverse Event | OMNARIS Nasal Spray 200 mcg Once Daily (N =380) % | Placebo (N = 369) %
Headache | 6.6 | 5.7
Nasopharyngitis | 6.6 | 5.4
Pharyngolaryngeal pain | 3.4 | 3.3

Pediatric Patients Aged 2 to 5 Years:

Two controlled clinical studies 6 and 12 weeks in duration were conducted in the US and included a total of 258 patients 2 to 5 years of age with perennial allergic rhinitis, of which 183 were treated with OMNARIS Nasal Spray 200 mcg, 100 mcg or 25 mcg daily. The distribution of adverse events was similar to that seen in the 6 to 11 year old children.

OVERDOSAGE

There are no data available on the effects of acute or chronic overdosage with OMNARIS Nasal Spray. Because of low systemic bioavailability, acute overdosage is unlikely to require any therapy other than observation. A single oral dose of up to 10 mg of ciclesonide in healthy volunteers was well tolerated and serum cortisol levels were virtually unchanged in comparison with placebo treatment. Chronic overdosage with any corticosteroid may result in signs or symptoms of hypercorticism (See PRECAUTIONS).

DOSAGE AND ADMINISTRATION

Seasonal Allergic Rhinitis

Adults and Children (6 Years of Age and Older): The recommended dose of OMNARIS Nasal Spray is 200 mcg per day administered as 2 sprays (50 mcg/spray) in each nostril once daily.

Perennial Allergic Rhinitis

Adults and Adolescents (12 Years of Age and Older): The recommended dose of OMNARIS Nasal Spray is 200 mcg per day administered as 2 sprays (50 mcg/spray) in each nostril once daily.

The maximum total daily dosage should not exceed 2 sprays in each nostril (200 mcg/day).

Prior to initial use, OMNARIS Nasal Spray must be gently shaken and then the pump must be primed by actuating eight times. If the product is not used for four consecutive days, it should be gently shaken and reprimed with one spray or until a fine mist appears.

Directions for Use

Illustrated patient's instructions for proper use accompany each package of OMNARIS Nasal Spray.

HOW SUPPLIED

OMNARIS is supplied in an amber glass bottle and provides for nasal delivery with a manual metered pump. OMNARIS Nasal Spray is supplied with an oxygen absorber sachet and enclosed in a foil pouch. OMNARIS Nasal Spray provides 120 metered sprays after initial priming. Each spray delivers 50 mcg of ciclesonide from the nasal actuator. The OMNARIS Nasal Spray bottle has been filled with an excess to accommodate the priming activity. The bottle should be discarded after removal from the foil pouch either after 120 sprays following initial priming (since the amount of ciclesonide delivered per spray thereafter may be substantially less than the labeled dose) or after 4 months. Patient instructions are also provided.

OMNARIS Nasal Spray 50 mcg, 120 metered sprays; net fill weight 12.5 g. (NDC 54868-6020-0)

Store at 25°C (77°F); excursions permitted to 15-30°C (59-86°F) [See USP Controlled Room Temp]. Do not freeze. Shake gently before use. Do not spray in eyes. Keep out of reach of children.

Manufactured for:

Sepracor Inc.
Marlborough, MA 01752 USA

Made in Germany

For customer service, call 1-888-394-7377
To report adverse events, call 1-877-737-7226
For medical information, call 1-800-739-0565

November 2007

USA F.1/1207/3.5472.73

Relabeling of "Additional Barcode" by:
Physicians Total Care, Inc.
Tulsa, OK 74146

Patient's Instructions for Use

OMNARIS (ciclesonide) Nasal Spray, 50 mcg

FOR INTRANASAL ADMINISTRATION ONLY

Please read this leaflet carefully before taking OMNARIS Nasal Spray. This leaflet does not contain the complete information about this medication. If you have any questions about OMNARIS Nasal Spray, ask your health care provider or pharmacist.

What you should know about OMNARIS Nasal Spray.

Your healthcare provider has prescribed OMNARIS Nasal Spray. It contains a medicine called ciclesonide, which helps relieve inflammation. This medication is used for the treatment of nasal symptoms associated with seasonal nasal allergy in adults and children 6 years of age and older and year-round nasal allergy in adults and adolescents 12 years of age and older.

The nasal spray delivers your medication as an aqueous spray. Once you begin treatment, use your nasal spray once a day, every day, as prescribed by your health care provider. OMNARIS Nasal Spray may begin to work within 24 hours after the first dose. Further symptom improvements may occur over 1 to 2 weeks for seasonal allergy symptoms and 5 weeks for year-round allergy symptoms. If your symptoms do not improve in that time frame or if your condition worsens, contact your health care provider.

Dosage

For Adults and Children (6 Years of Age and Older) with seasonal allergy symptoms: The recommended dose is 2 sprays in each nostril once daily.

For Adults and Adolescents (12 Years of Age and Older) with year-round allergy symptoms: The recommended dose is 2 sprays in each nostril once daily.

You should not use more than a total of 2 sprays in each nostril daily.

Preparing For Use

1. Remove OMNARIS Nasal Spray from its foil pouch. Count 4 months from this date and write this date (that is 4 months from removing the bottle from the foil pouch) on the sticker provided on the carton. Peel off this sticker and place it in the space provided on your nasal spray bottle. It's important to throw away the nasal spray bottle after this date.
2. Before the first use, shake the bottle gently and prime the pump by pressing downward on the shoulders of the applicator eight times. Read the complete instructions carefully and use only as directed. If you have not used the nasal spray for 4 days, shake the bottle gently and prime the pump again by spraying one time or until a fine mist appears.

Using the Spray

1. Blow your nose to clear your nostrils if needed.

2. Shake the bottle gently and remove the dust cap.

3. Hold the bottle firmly with your index and middle finger on either side of the spray tip while supporting the base of the bottle with your thumb (Figure 1).

Figure 1.

4. Insert spray tip into one nostril, and close the other nostril with your finger (Figure 2).

Figure 2.

5. Tilt your head forward slightly and keeping the bottle upright, press the pump quickly and firmly and inhale through your nose as you spray (Figure 3). Avoid spraying in eyes or directly onto the nasal septum (the wall between the two nostrils).

Figure 3.

6. Repeat steps 3-5 for the second spray in the same nostril and for each spray in the other nostril.

Storage Instructions

Keep your nasal spray clean and dry at all times. Store medication between 59° and 86° F. Do not freeze. Keep out of the reach of young children.

How To Know When Your Nasal Spray Bottle Is Empty

The amount of nasal spray left can be seen through a window on the bottle. Do not use this bottle for more than the labeled number of sprays or after the "discard by date" you wrote on the sticker when you opened the foil pouch. You may want to obtain a refill before your supply runs out if recommended by your health care provider.

Applicator Cleaning Instructions

After daily use of your nasal spray, wipe the applicator tip with a clean tissue and replace the dust cap.

If the nasal applicator is clogged or requires more thorough cleaning, use the following cleaning instructions (Do not try to unblock the tiny spray hole on the nasal applicator with a pin or other sharp object):

1. Remove the dust cap and then gently pull upwards to free the nasal applicator.
2. Wash the dust cap and applicator with warm water.
3. Dry and replace the nasal applicator.
4. Prime the unit with one spray or until a fine mist appears.
5. Replace the dust cap.

Further Information

Avoid spraying in eyes or directly onto the nasal septum (the wall between the two nostrils).

This leaflet does not contain the complete information about your medicine. If you have any questions or are not sure about something, then you should ask your doctor or pharmacist.

You may want to read this leaflet again. Please DO NOT THROW IT AWAY until you have finished your medicine.

Manufactured for:

Sepracor Inc.
Marlborough, MA 01752 USA

Made in Germany

For customer service, call 1-888-394-7377
To report adverse events, call 1-877-737-7226
For medical information, call 1-800-739-0565

November 2007

USA F.1/1207/3.5472.82

PRINCIPAL DISPLAY PANEL

OMNARIS (ciclesonide) Nasal Spray, 50 mcg